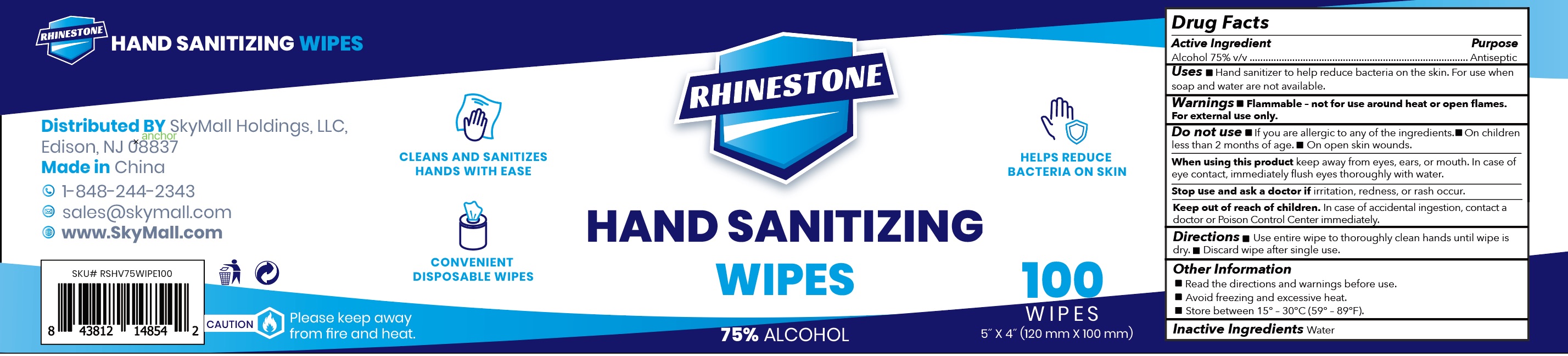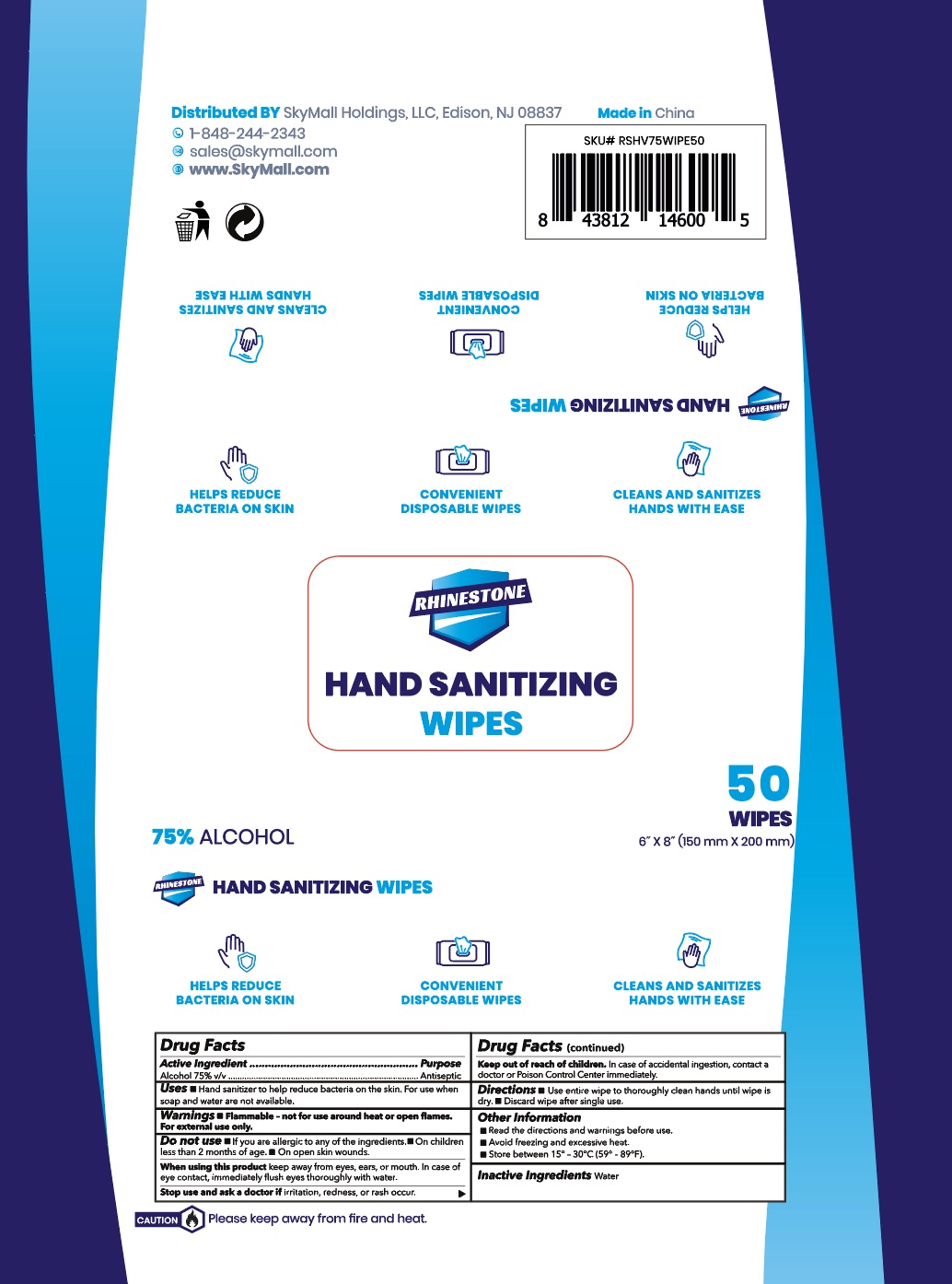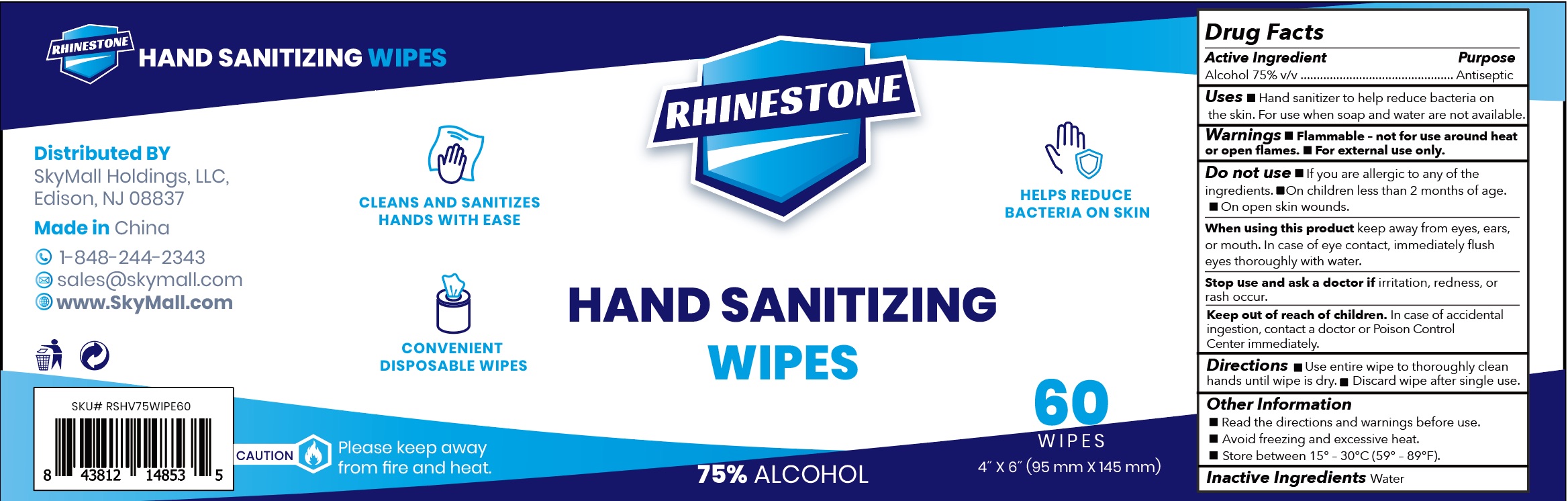 DRUG LABEL: Hand Sanitizer Wipes
NDC: 80230-008 | Form: CLOTH
Manufacturer: Skymall Holdings LLC
Category: otc | Type: HUMAN OTC DRUG LABEL
Date: 20200922

ACTIVE INGREDIENTS: ALCOHOL 75 mL/100 1
INACTIVE INGREDIENTS: WATER

Rhinestone wipes 75 Alc

Active Ingredient

Alcohol 75%

Purpose

Antiseptic

Use

■ Hand sanitizer to help reduce bacteria on the skin. For use when soap and water are not available

Warnings

■ Flammable- not for use around heat or open flames. For external use only.

Do not use

■ if you are allergic to any of the ingredients. ■ On children less than 2 months of age. ■ On open skin wounds

When using this product

keep away from eyes, ears or mouth. In case of eye contact, immediately flush eyes thoroughly with water.

Stop use and ask a doctor if

irritation, redness or rash occur.

Keep out of reach of children

In case of accidental ingestion, contact a doctor or Poison Control Center immediately.

Directions

■ Use entire wipe to thoroughly clean hands until wipe is dry. ■ Discard wipe after single use.

Other information

■ Read the directions and warnings before use.

■ Avoid freezing and excessive heat.

■ Store between 15º -30ºC (59º -89ºF)

Inactive Ingredients

Water